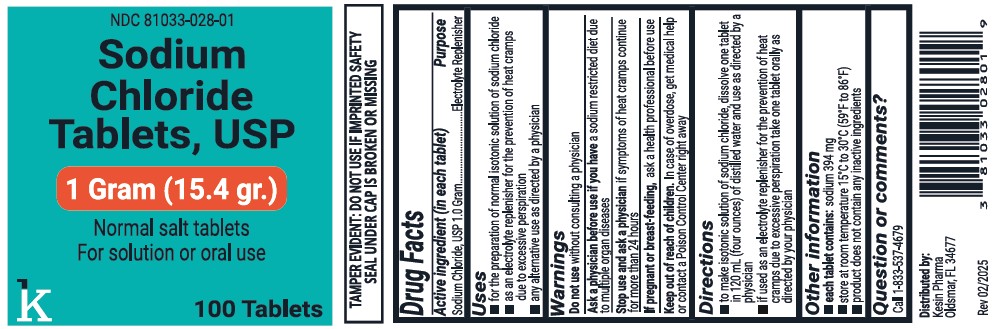 DRUG LABEL: Sodium Chloride
NDC: 81033-028 | Form: TABLET
Manufacturer: Kesin Pharma Corporation
Category: otc | Type: HUMAN OTC DRUG LABEL
Date: 20251117

ACTIVE INGREDIENTS: SODIUM CHLORIDE 1000 mg/1 1

SODIUM CHLORIDE TABLETS, USP 1 Gram (15.4 gr.)

DRUG FACTS

Active ingredient (in each tablet)

Sodium Chloride, USP 1 Gram

Purpose

Electrolyte Replenisher

USES

- for the preparation of normal isotonic solution of sodium chloride
- as an electrolyte replenisher for the prevention of heat cramps due to excessive perspiration
- any alternative use as directed by a physician

WARNINGS

Do not use without consulting a physician

Ask a physician before use if you have a sodium restricted diet due to multiple organ diseases

Stop use and ask a physician if symptoms of heat cramps continue for more than 24 hours

If pregnant or breast-feeding, ask a health professional before use

Keep out of reach of children.

Overdose

In case of overdose, get medical help or contact a Poison Control Center right away

DIRECTIONS

- to make isotonic solution of sodium chloride, dissolve one tablet in 120 mL (four ounces) of distilled water and use as directed by a physician
- if used as an electrolyte replenisher for the prevention of heat cramps due to excessive perspiration take one tablet orally as directed by your physician.

OTHER INFORMATION

- each tablet contains: sodium 394 mg
- store at room temperature 15ºC to 30ºC (59ºF to 86ºF)

Inactive Ingredients

- product does not contain any inactive ingredients

QUESTIONS OR COMMENTS?

Call 1-833-537-4679

Distributed by:

Kesin Pharma

Oldsmar, FL 34677

Rev 02/2025

PACKAGE LABEL

Sodium Chloride Tablets, USP

1 Gram (15.4 gr.)

Normal salt tablets

For solution or oral use

100 Tablets